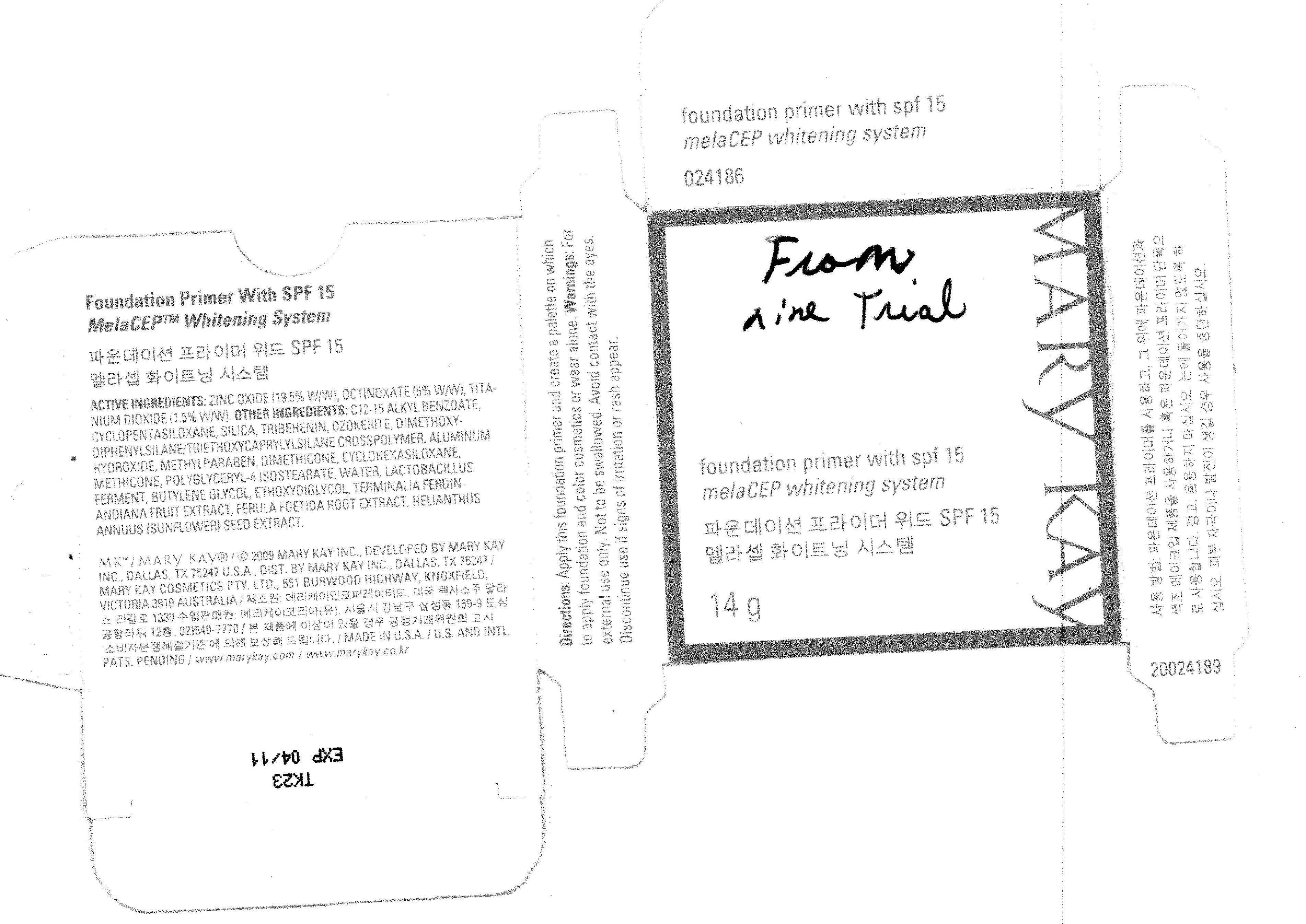 DRUG LABEL: Foundation Primer SPF 15
NDC: 51531-4189 | Form: CREAM
Manufacturer: Mary Kay Inc.
Category: otc | Type: HUMAN OTC DRUG LABEL
Date: 20110308

ACTIVE INGREDIENTS: Titanium Dioxide 0.222 g/14 g; ZINC OXIDE 2.73 g/14 g; Octinoxate 0.7 g/14 g
INACTIVE INGREDIENTS: ALKYL (C12-15) BENZOATE; CYCLOMETHICONE 5; SILICON DIOXIDE; Tribehenin; CERESIN; TRIETHOXYCAPRYLYLSILANE; Aluminum Hydroxide; Methylparaben; Dimethicone; CYCLOMETHICONE 6; Polyglyceryl-4 Isostearate; Water; Butylene Glycol; DIETHYLENE GLYCOL MONOETHYL ETHER; FRUIT; FERULA ASSA-FOETIDA ROOT; SUNFLOWER SEED

ACTIVE INGREDIENT

ACTIVE INGREDIENTS: ZINC OXIDE (19.5% W/W), OCTINOXATE(5% W/W) , TITANIUM DIOXIDE (1.5% W/W)

WARNINGS

Warnings; Contains OXYBENZONE. For external use only. Not to be swallowed. Avoid contact with the eyes. Discontinue use if signs of irritation or rash appear.

INDICATIONS AND USAGE

Directions; In the morning , after applying Essence , apply Day Moisturizer With SPF 15 liberally over face and neck.